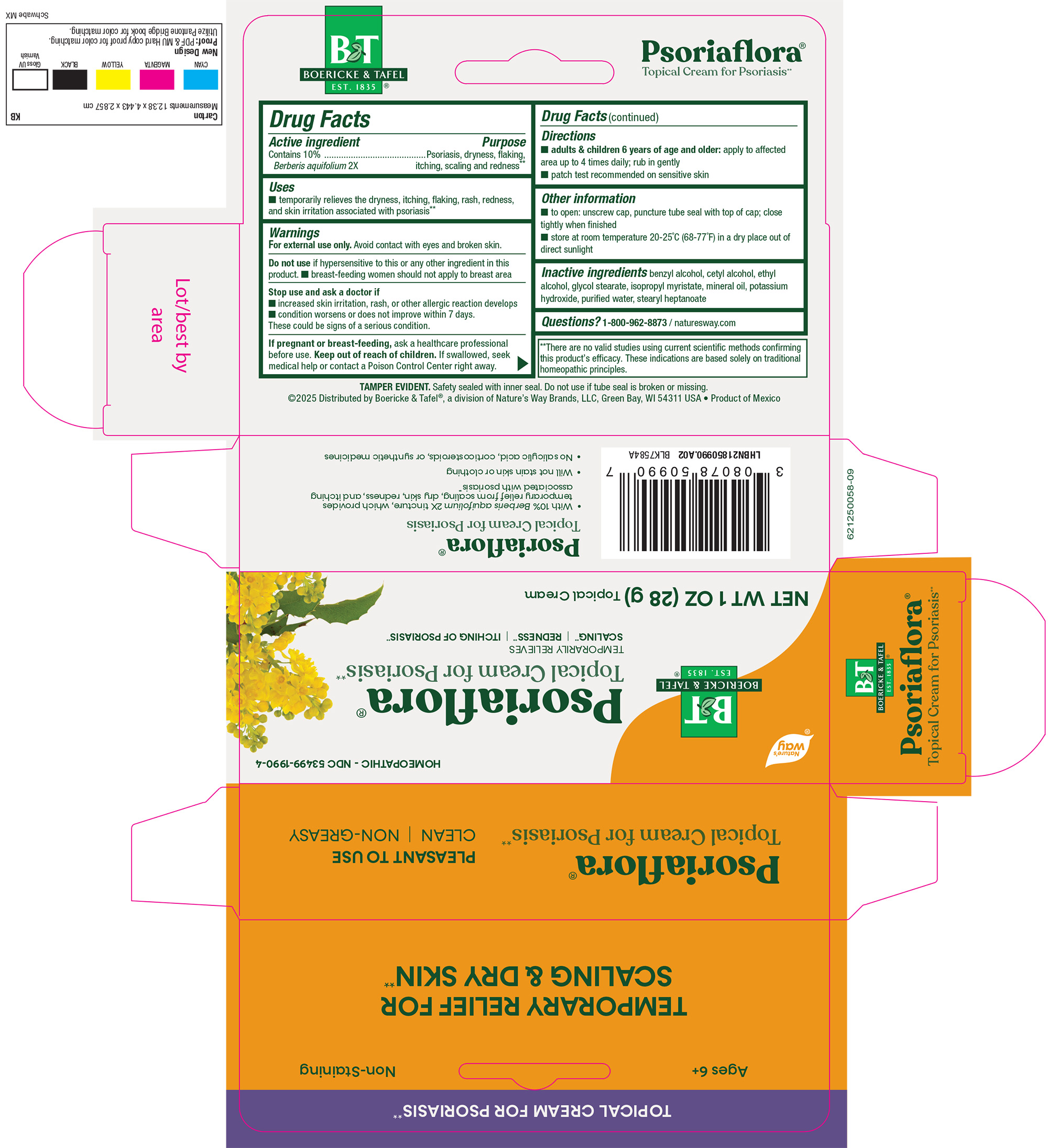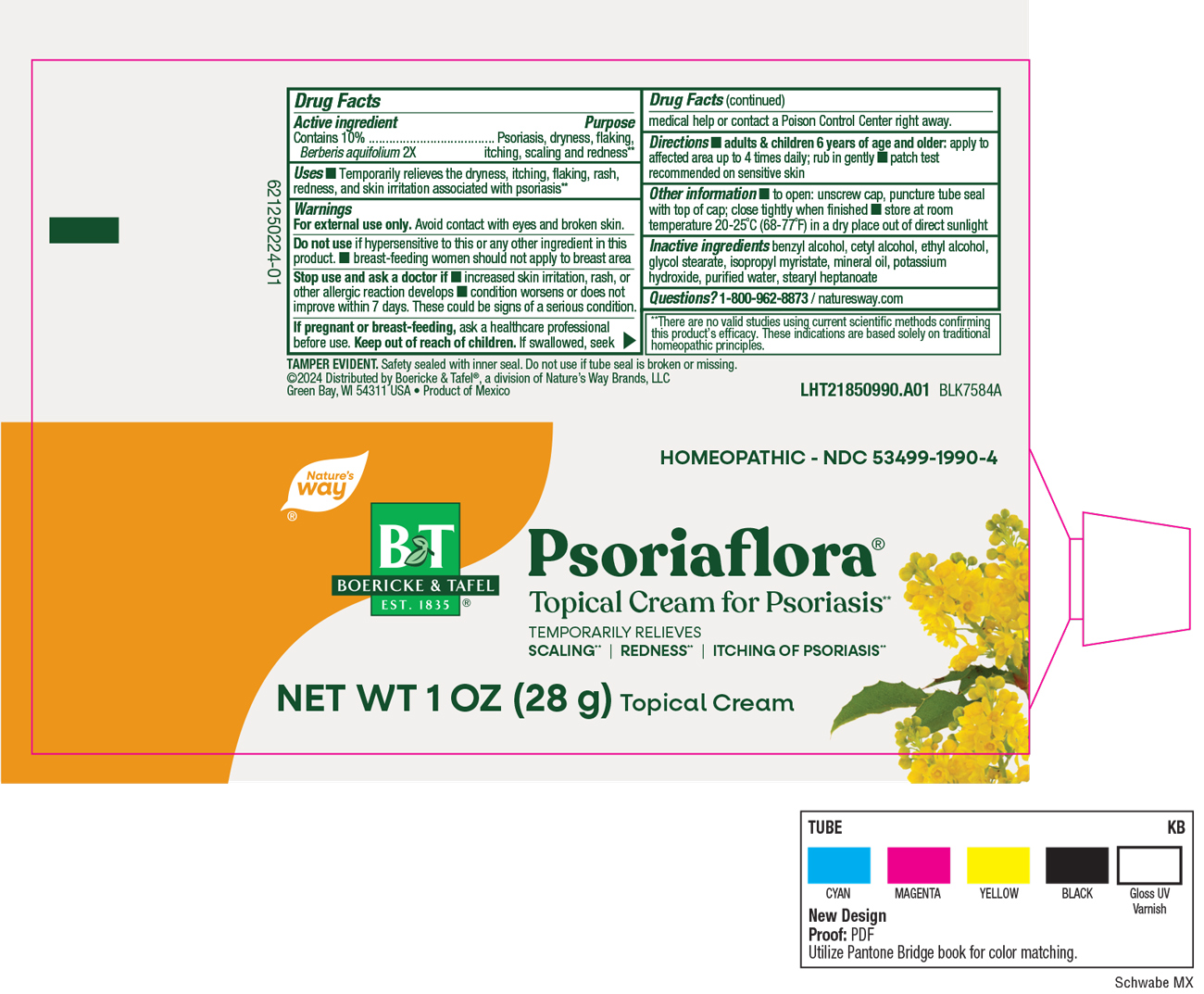 DRUG LABEL: PSORIAFLORA
NDC: 53499-1990 | Form: CREAM
Manufacturer: Schwabe North America, Inc
Category: homeopathic | Type: HUMAN OTC DRUG LABEL
Date: 20250815

ACTIVE INGREDIENTS: MAHONIA AQUIFOLIUM ROOT BARK 2 [hp_X]/28 g
INACTIVE INGREDIENTS: BENZYL ALCOHOL; CETYL ALCOHOL; ALCOHOL; GLYCOL STEARATE; ISOPROPYL MYRISTATE; MINERAL OIL; POTASSIUM HYDROXIDE; WATER; STEARYL HEPTANOATE

Psoriaflora Cream

Active Ingredient

Berberis aquifolium 2X

Inactive Ingredient

Benzyl Alcohol

Cetyl Alcohol

Ethyl Alcohol

Glycol Stearate

Isopropyl Myristate

Mineral Oil

Potassium Hydroxide

Purified Water

Stearyl Heptanoate

Dosage & Administration

Directions:

Adults and Children 6 years of age and older: apply to affected area up to 4 times daily. Rub in gently.

Patch test recommended on sensitive skin.

Indications & Usage

Temporarily relieves the dryness, itching, flaking, rash, redness, and skin irritation associated with psoriasis.

Purpose

Temporarily relieves the dryness, itching, flaking, rash, redness ,and skin irritation associated with psoriasis.

Warnings

For external use only.

Avoid contact with eyes and broken skin.

Do not use if hypersensitive to this or any other ingredient in this product.

Breast-feeding women should not apply to breast area.

Stop Use

Stop use and ask a doctor if increased skin irritation, rash, or other allergic reaction develops, condition worsens or does not improve within 7 days.

These could be signs of a serious condition.

Pregnancy or breast feeding

If pregnant or breast-feeding, ask a healthcare professional before use.

Keep out of reach of children

Overdosage

If swallowed, seek medical help or contact a Poison Control Center right away.